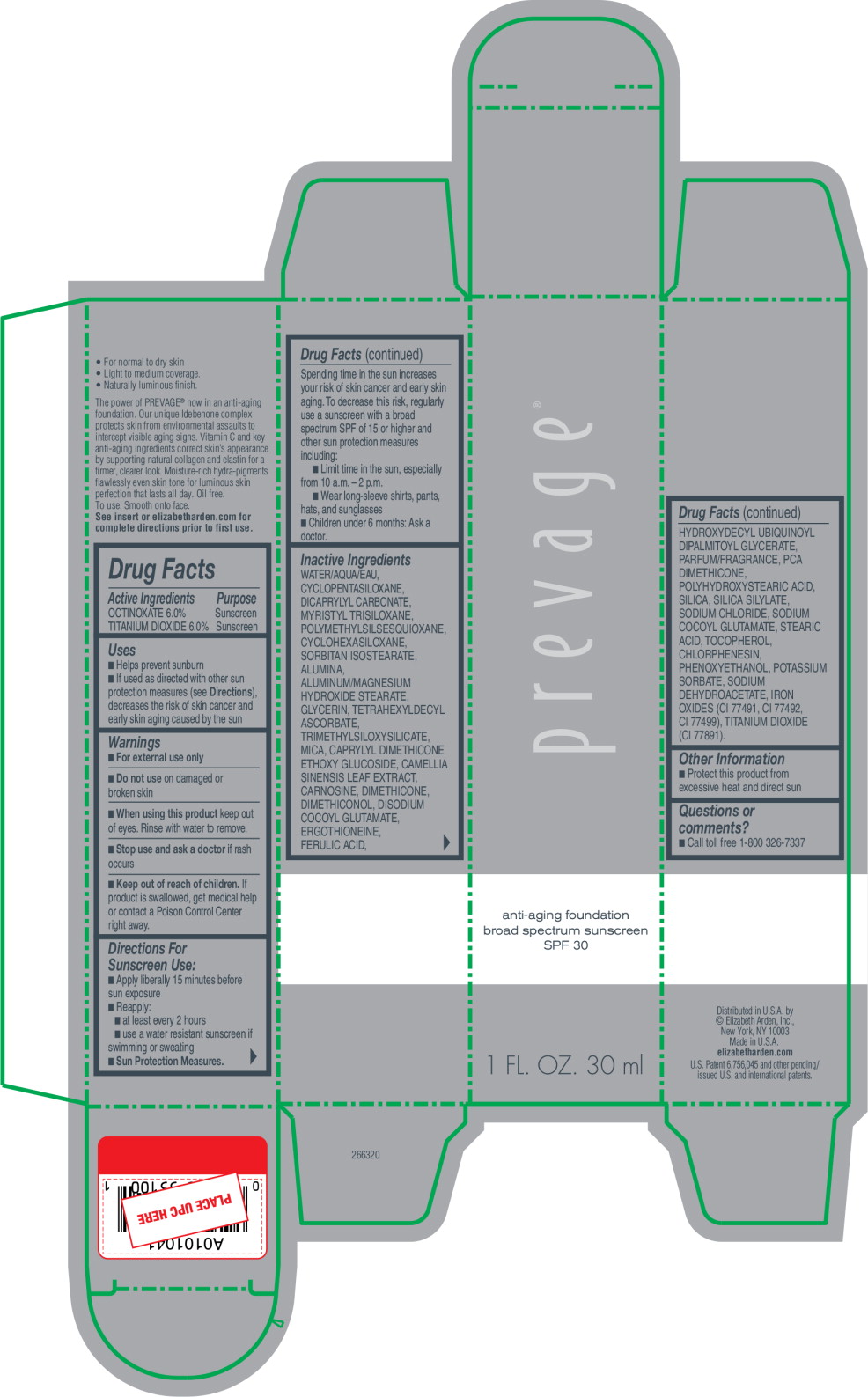 DRUG LABEL: ELIZABETH ARDEN PREVAGE ANTI-AGING FOUNDATION BROAD SPECTRUM SUNSCREEN SPF 30
NDC: 67938-3051 | Form: LOTION
Manufacturer: ELIZABETH ARDEN, INC
Category: otc | Type: HUMAN OTC DRUG LABEL
Date: 20170801

ACTIVE INGREDIENTS: OCTINOXATE .06 g/1 mL; TITANIUM DIOXIDE .06 g/1 mL
INACTIVE INGREDIENTS: WATER; CYCLOMETHICONE 5; DICAPRYLYL CARBONATE; MYRISTYL TRISILOXANE; CYCLOMETHICONE 6; SORBITAN ISOSTEARATE; ALUMINUM OXIDE; GLYCERIN; TETRAHEXYLDECYL ASCORBATE; MICA; GREEN TEA LEAF; CARNOSINE; DIMETHICONE; DISODIUM COCOYL GLUTAMATE; ERGOTHIONEINE; FERULIC ACID; HYDROXYDECYL UBIQUINOYL DIPALMITOYL GLYCERATE; SILICON DIOXIDE; SODIUM CHLORIDE; SODIUM COCOYL GLUTAMATE; STEARIC ACID; TOCOPHEROL; CHLORPHENESIN; PHENOXYETHANOL; POTASSIUM SORBATE; SODIUM DEHYDROACETATE; FERRIC OXIDE RED; FERRIC OXIDE YELLOW; FERROSOFERRIC OXIDE

Drug Facts

Active Ingredients

OCTINOXATE 6.0%

TITANIUM DIOXIDE 6.0%

Purpose

Sunscreen

Sunscreen

Uses

- Helps prevent sunburn
- If used as directed with other sun protection measures (see Directions), decreases the risk of skin cancer and early skin aging caused by the sun

Warnings

- For external use only

- Do not use on damaged or broken skin

- When using this product keep out of eyes. Rinse with water to remove.

- Stop use and ask a doctor if rash occurs

- Keep out of reach of children. If product is swallowed, get medical help or contact a Poison Control Center right away.

Directions For Sunscreen Use:

- Apply liberally 15 minutes before sun exposure
- Reapply:
  - at least every 2 hours
  - use a water resistant sunscreen if swimming or sweating
- Sun Protection Measures.
  Spending time in the sun increases your risk of skin cancer and early skin aging. To decrease this risk, regularly use a sunscreen with a broad spectrum SPF of 15 or higher and other sun protection measures including:
  - Limit time in the sun, especially from 10 a.m. – 2 p.m.
  - Wear long-sleeve shirts, pants, hats, and sunglasses
- Children under 6 months: Ask a doctor.

Inactive Ingredients

WATER/AQUA/EAU, CYCLOPENTASILOXANE, DICAPRYLYL CARBONATE, MYRISTYL TRISILOXANE, POLYMETHYLSILSESQUIOXANE, CYCLOHEXASILOXANE, SORBITAN ISOSTEARATE, ALUMINA, ALUMINUM/MAGNESIUM HYDROXIDE STEARATE, GLYCERIN, TETRAHEXYLDECYL ASCORBATE, TRIMETHYLSILOXYSILICATE, MICA, CAPRYLYL DIMETHICONE ETHOXY GLUCOSIDE, CAMELLIA SINENSIS LEAF EXTRACT, CARNOSINE, DIMETHICONE, DIMETHICONOL, DISODIUM COCOYL GLUTAMATE, ERGOTHIONEINE, FERULIC ACID, HYDROXYDECYL UBIQUINOYL DIPALMITOYL GLYCERATE, PARFUM/FRAGRANCE, PCA DIMETHICONE, POLYHYDROXYSTEARIC ACID, SILICA, SILICA SILYLATE, SODIUM CHLORIDE, SODIUM COCOYL GLUTAMATE, STEARIC ACID, TOCOPHEROL, CHLORPHENESIN, PHENOXYETHANOL, POTASSIUM SORBATE, SODIUM DEHYDROACETATE, IRON OXIDES (CI 77491, CI 77492, CI 77499), TITANIUM DIOXIDE (CI 77891).

Other Information

- Protect this product from excessive heat and direct sun

Questions or comments?

- Call toll free 1-800 326-7337

Principal Display Panel - Prevage Anti-Aging Foundation Carton Label

prevage®

anti-aging foundation

broad spectrum sunscreen

SPF 30

1 FL. OZ. 30 ml